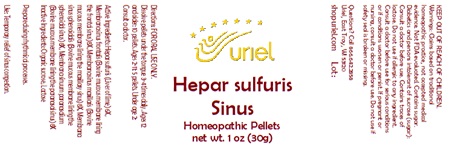 DRUG LABEL: Hepar sulfuris Sinus
NDC: 48951-5050 | Form: PELLET
Manufacturer: Uriel Pharmacy Inc.
Category: homeopathic | Type: HUMAN OTC DRUG LABEL
Date: 20251106

ACTIVE INGREDIENTS: CALCIUM SULFIDE 6 [hp_X]/1 1; BOS TAURUS NASAL MUCOSA 8 [hp_X]/1 1
INACTIVE INGREDIENTS: SUCROSE

Hepar sulfuris Sinus

INDICATIONS AND USAGE

Directions: FOR ORAL USE ONLY.

DOSAGE AND ADMINISTRATION

Dissolve pellets under the tongue 3-4
times daily. Ages 12 and older: 10 pellets.
Ages 2-11: 5 pellets. Under age 2: Consult
a doctor.

ACTIVE INGREDIENT

Active Ingredients: Hepar sulfuris (Liver of lime) 6X, Membrana sinus frontalis (Bovine mucous membrane lining the frontal sinus) 8X, Membrana sinus maxillaris (Bovine mucous membrane lining the maxillary sinus) 8X, Membrana sinus sphenoidalis (Bovine mucous membrane lining the sphenoidal sinus) 8X, Membrana sinuum paranasalium (Bovine mucous membrane lining the paranasal sinus) 8X

Inactive Ingredients: Organic sucrose, Lactose

Prepared using rhythmical processes.

PURPOSE

Use: Temporary relief of sinus congestion.

KEEP OUT OF REACH OF CHILDREN.

WARNINGS

Warnings: Claims based on traditional homeopathic practice, not accepted medical evidence. Not FDA evaluated. Contains sugar. Diabetics and persons intolerant of sucrose (sugar): Consult a doctor before use. Contains traces of lactose. Do not use if allergic to any ingredient. Consult a doctor before use for serious conditions or if conditions worsen or persist. If pregnant or nursing, consult a doctor before use. Do not use if safety seal is broken or missing.

Questions? Call 866.642.2858
Uriel, East Troy, WI 53120
shopuriel.com